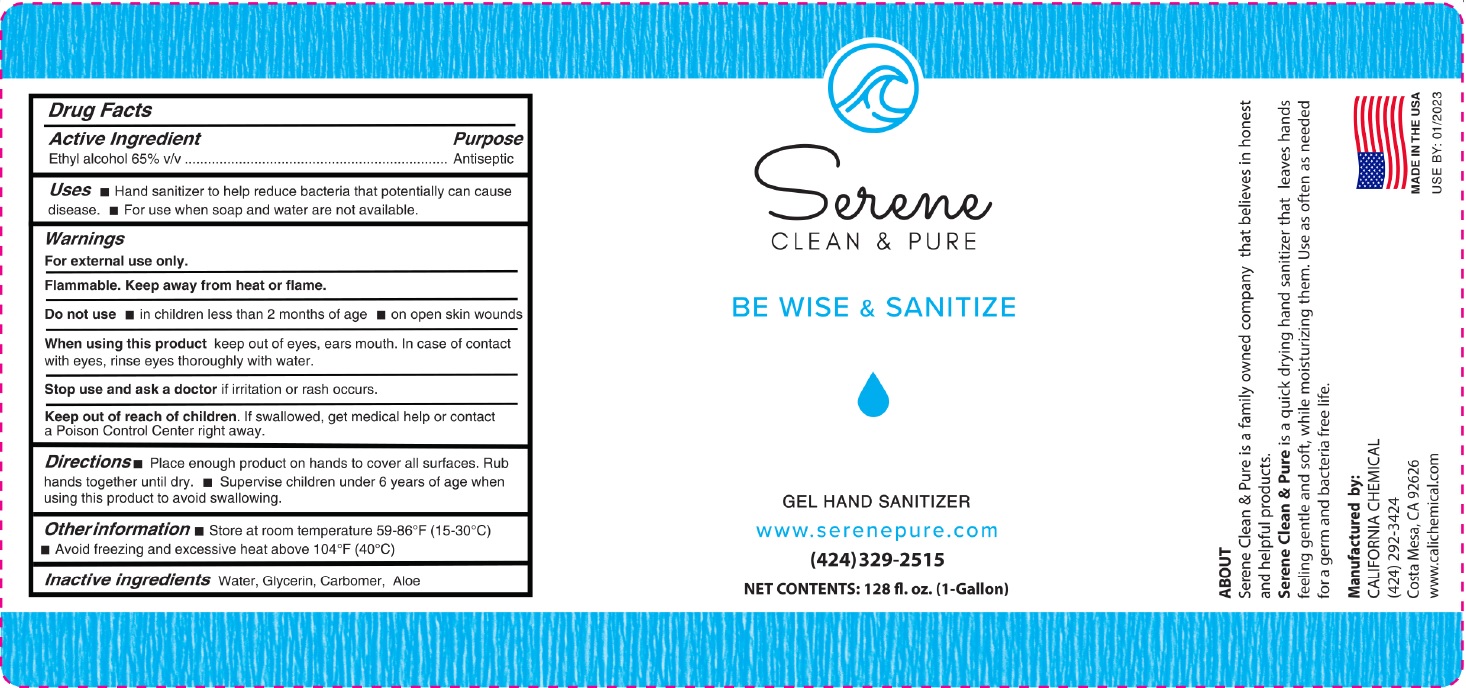 DRUG LABEL: Serene Clean and Pure Hand Sanitizer Gel
NDC: 78643-300 | Form: GEL
Manufacturer: Serene Clean & Pure LLC
Category: otc | Type: HUMAN OTC DRUG LABEL
Date: 20210101

ACTIVE INGREDIENTS: ALCOHOL 65 mL/100 mL
INACTIVE INGREDIENTS: ALOE VERA LEAF; GLYCERIN; WATER; CARBOMER HOMOPOLYMER, UNSPECIFIED TYPE

Serene Clean & Pure Ethanol Gel Hand Sanitizer

Active ingredient

Ethyl Alcohol 65% v/v.

Purpose

Antiseptic

Use

Hand Sanitizer to help reduce bacteria that potentially can cause disease. For use when soap and water are not available.

Warnings

For external use only. Flammable. Keep away from heat or flame

Do not use

- in children less than 2 months of age
- on open skin wounds

When using this product

keep out of eyes, ears, and mouth. In case of contact with eyes, rinse eyes thoroughly with water.

Stop use and ask a doctor

if irritation or rash occurs. These may be signs of a serious condition.

Keep out of reach of children.

If swallowed, get medical help or contact a Poison Control Center right away.

Directions

- Place enough product on hands to cover all surfaces. Rub hands together until dry.
- Supervise children under 6 years of age when using this product to avoid swallowing.

Other information

- Store between 15-30C (59-86F)
- Avoid freezing and excessive heat above 40C (104F)

Inactive ingredients

Water, glycerin, carbomer, aloe

Package Label - Principal Display Panel

Serene Clean & Pure

Be Wise & Sanitize

Gel Hand Sanitizer

www.serenepure.com

(424) 329-2515

ABOUT

Serene Clean & Pure is a family owned company that believes in honest and helpful products.

Serene Clean & Pure is a quickly drying hand sanitizer that leaves hands feeling gentle and soft, while moisturizing them. Use as often as needed for a germ and bacteria free life

Manufactured by:

CALIFORNIA CHEMICAL

(424) 292-3424

Costa Mesa, CA 92626

www.calichemical.com